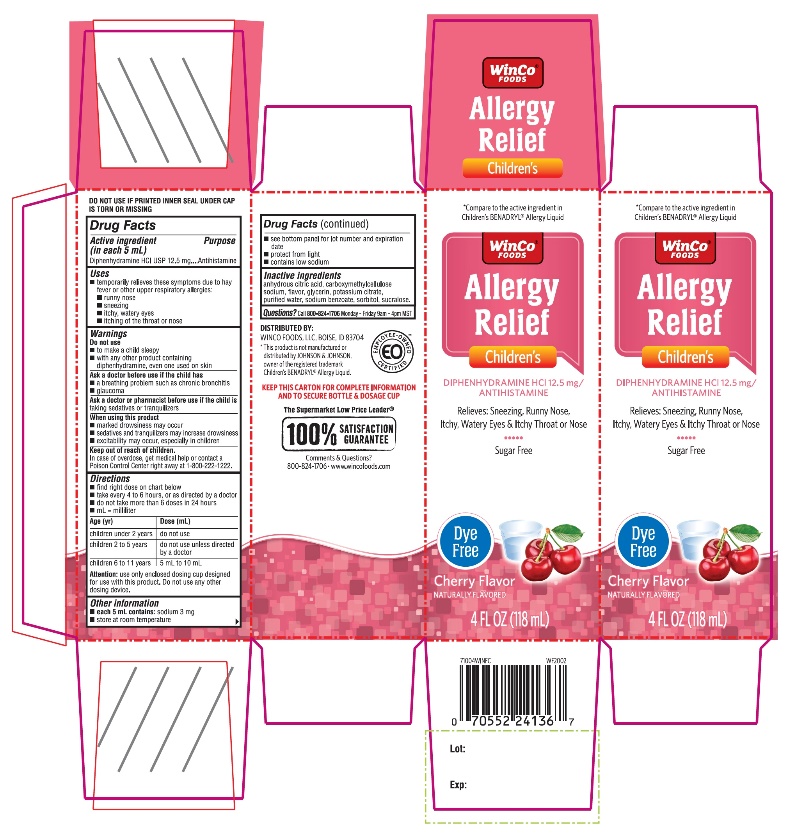 DRUG LABEL: Winco Foods Childrens Allergy Relief

NDC: 67091-354 | Form: SOLUTION
Manufacturer: WINCO FOODS, LLC
Category: otc | Type: HUMAN OTC DRUG LABEL
Date: 20251202

ACTIVE INGREDIENTS: DIPHENHYDRAMINE HYDROCHLORIDE 12.5 mg/5 mL
INACTIVE INGREDIENTS: ANHYDROUS CITRIC ACID; CARBOXYMETHYLCELLULOSE SODIUM, UNSPECIFIED; GLYCERIN; POTASSIUM CITRATE; WATER; SODIUM BENZOATE; SORBITOL; SUCRALOSE

Winco Food Dye-Free Children’s Allergy Relief Cherry Flavor 4 FL OZ 118 mL

Drug Facts

Active ingredient (in each 5 mL)

Diphenhydramine HCl USP 12.5 mg

Purpose

Antihistamine

Uses

- temporarily relieves these symptoms due to hay fever or other upper respiratory allergies:
  - runny nose
  - sneezing
  - itchy, watery eyes
  - itching of the throat or Nose

Warnings

Do not use

- to make a child sleepy
- with any other product containing diphenhydramine, even one used on skin

Ask a doctor before use if the child has

- a breathing problem such as chronic bronchitis
- glaucoma

Ask a doctor or pharmacist before use if the child istaking sedatives or tranquilizers

When using this product

- marked drowsiness may occur
- sedatives and tranquilizers may increase drowsiness
- excitability may occur, especially in children

Keep out of reach of children.

In case of overdose, get medical help or contact a Poison Control Center right away at (1-800-222-1222)

Directions

- find right dose on chart below
- take every 4 to 6 hours, or as directed by a doctor
- do not take more than 6 doses in 24 hours
- mL = milliliter

Age (yr) | Dose (mL)
children under 2 years | do not use
children 2 to 5 years | do not use unless directed by a doctor
children 6 to 11 years | 5 mL to 10 mL

Attention:use only enclosed dosing cup designed for use with this product. Do not use any other dosing device.

Other information

- each 5 mL contains:sodium 3 mg
- store at room temperature
- see bottom panel for lot number and expiration date
- protect from light
- contains low sodium

Inactive ingredients

anhydrous citric acid, carboxymethylcellulose sodium, flavors, glycerin, potassium citrate, purified water, sodium benzoate, sorbitol, sucralose.

Questions or comments?

1-866-467-2748

PRINCIPAL DISPLAY PANEL

*Compare to Children's Benadryl®Dye-Free active ingredient

NDC 67091-354-18

Dye-Free

Children’s Allergy Relief

Diphenhydramine HCl USP ǀ Antihistamine
Oral solution

For Relief of:

1. Runny Nose,
2. Itchy Throat or Nose
3. Sneezing and
4. Itchy, Watery Eyes

Sugar-Free

Natural Cherry Flavor

4 FL. OZ. (118 mL)
TAMPER EVIDENT: DO NOT USE IF PRINTED INNER SEAL UNDER CAP IS TORN OR MISSING

*This product is not manufactured or distributed by Johnson and Johnson, owner of the registered trademark Children’s Benadryl®Dye–Free.

IMPORTANT:Keep this carton for the future reference on full labeling.

Distributed by:

WINCO FOODS, LLC, ID 83704